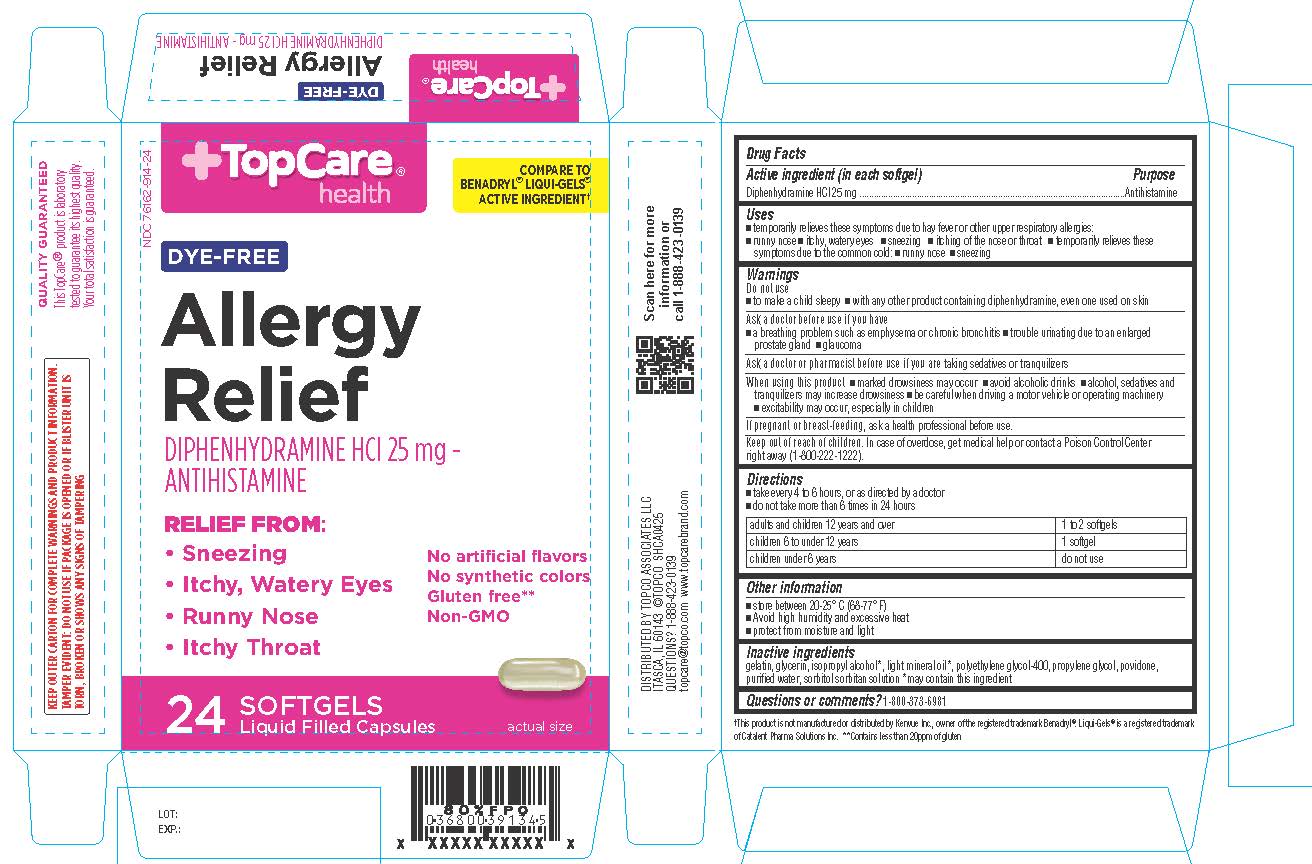 DRUG LABEL: Dye Free Allergy Relief
NDC: 76162-914 | Form: CAPSULE, LIQUID FILLED
Manufacturer: Topco Associates, LLC
Category: otc | Type: HUMAN OTC DRUG LABEL
Date: 20251031

ACTIVE INGREDIENTS: DIPHENHYDRAMINE HCL 25 mg/1 1
INACTIVE INGREDIENTS: POLYETHYLENE GLYCOL 400; PROPYLENE GLYCOL; POVIDONE; SORBITOL; SORBITAN; WATER; LIGHT MINERAL OIL; GELATIN; GLYCERIN; ISOPROPYL ALCOHOL

Dye Free Allergy Relief

Drug Facts

Active ingredient (in each softgel)

Diphenhydramine HCl 25 mg

Purpose

Antihistamine

Uses

- temporarily relieves these symptoms due to hay fever or other upper respiratory allergies:
- runny nose
- itchy, watery eyes
- sneezing
- itching of the nose or throat
- temporarily relieves these symptoms due to the common cold:
- runny nose
- sneezing

Warnings

Do not use

- to make a child sleepy
- with any other product containing diphenhydramine, even one used on skin

Ask a doctor before use if you have

- a breathing problem such as emphysema or chronic bronchitis
- trouble urinating due to an enlarged prostate gland
- glaucoma

Ask a doctor or pharmacist before use if you aretaking sedatives or tranquilizers

When using this product

- marked drowsiness may occur
- avoid alcoholic drinks
- alcohol, sedatives and
- tranquilizers may increase drowsiness
- be careful when driving a motor vehicle or operating machinery
- excitability may occur, especially in children

PREGNANCY OR BREAST FEEDING

If pregnant or breast-feeding,ask a health professional before use.

Keep out of reach of children.In case of overdose, get medical help or contact a Poison Control Center right away (1-800-222-1222).

Directions

- take every 4 to 6 hours, or as directed by a doctor
- do not take more than 6 times in 24 hours

adults & children 12 yrs & over | 1 to 2 Softgels
children 6 to under 12 yrs | 1 Softgel
children under 6 yrs | do not use

Other information

- store between 20-25° C (68-77° F)
- Avoid high humidity and excessive heat
- protect from moisture and light

Questions or comments?

1-800-373-6981 (toll-free)

Inactive ingredients

gelatin, glycerin, isopropyl alcohol*, light mineral oil*, polyethylene glycol-400, propylene glycol, povidone, purified water, sorbitol sorbitan solution *may contain this ingredient

Distributed by:
Topco Associates LLC
Itasca, IL 60143

PRINCIPAL DISPLAY PANEL

TopCare health

Dye-Free
Allergy Relief

Diphenhydramine HCl 25 mg

Relieves

- Sneezing
- Runny Nose
- Itchy, Watery Eyes
- Itchy Throat

Diphenhydramine HCl 25 mg
No artificial flavors
No synthetic colors
Gluten free*
Non-GMO

Carton